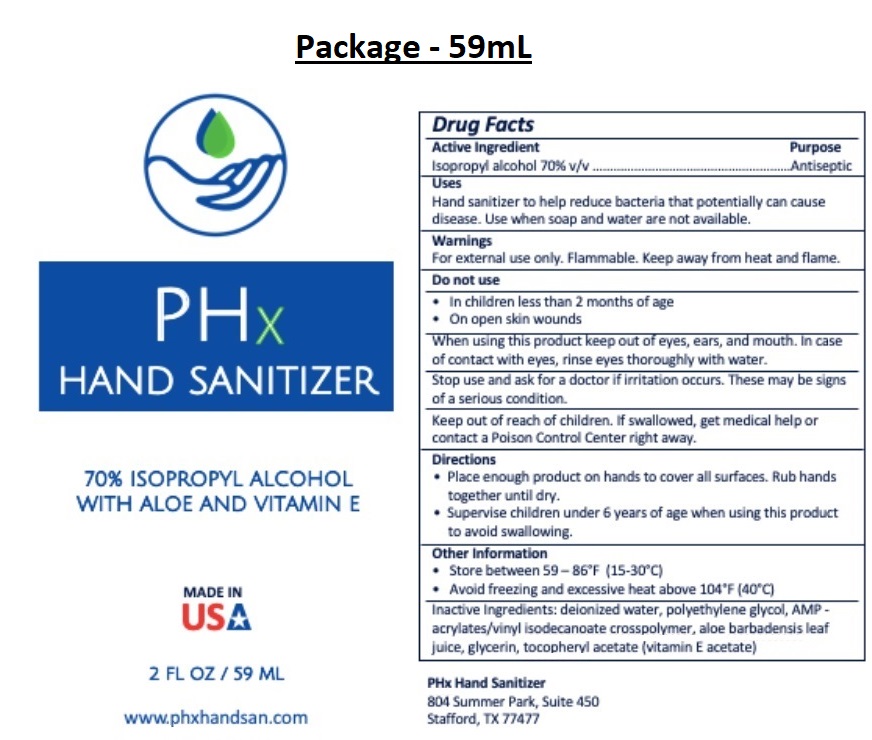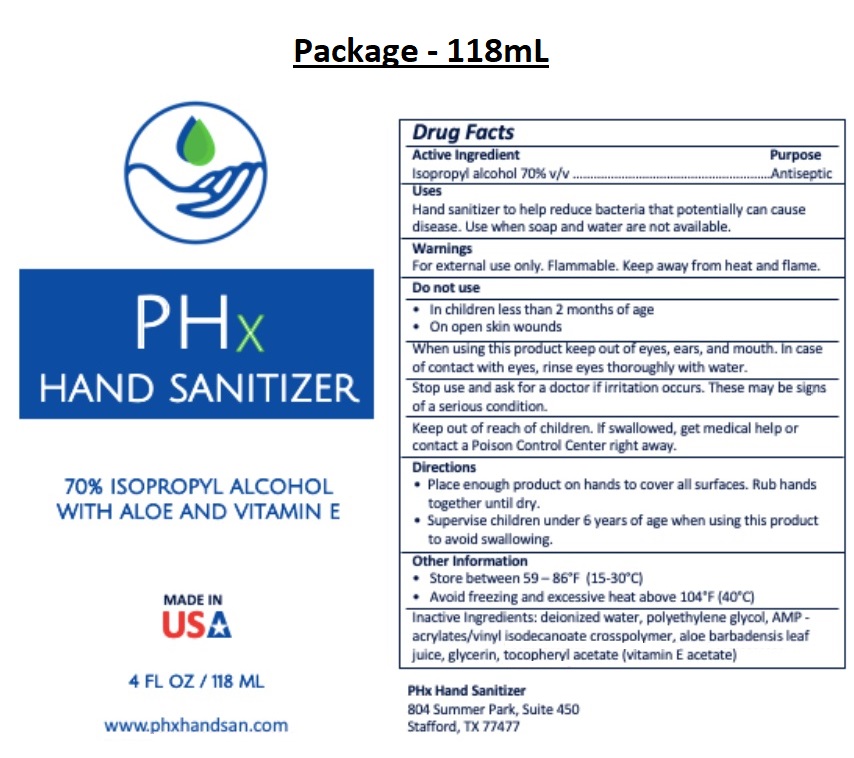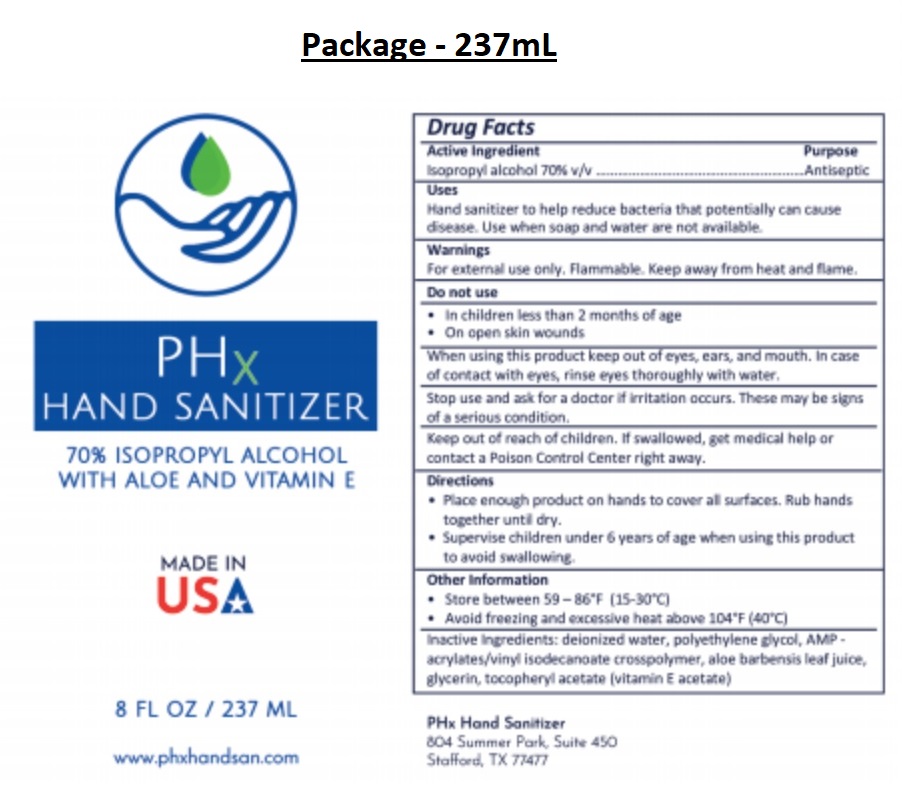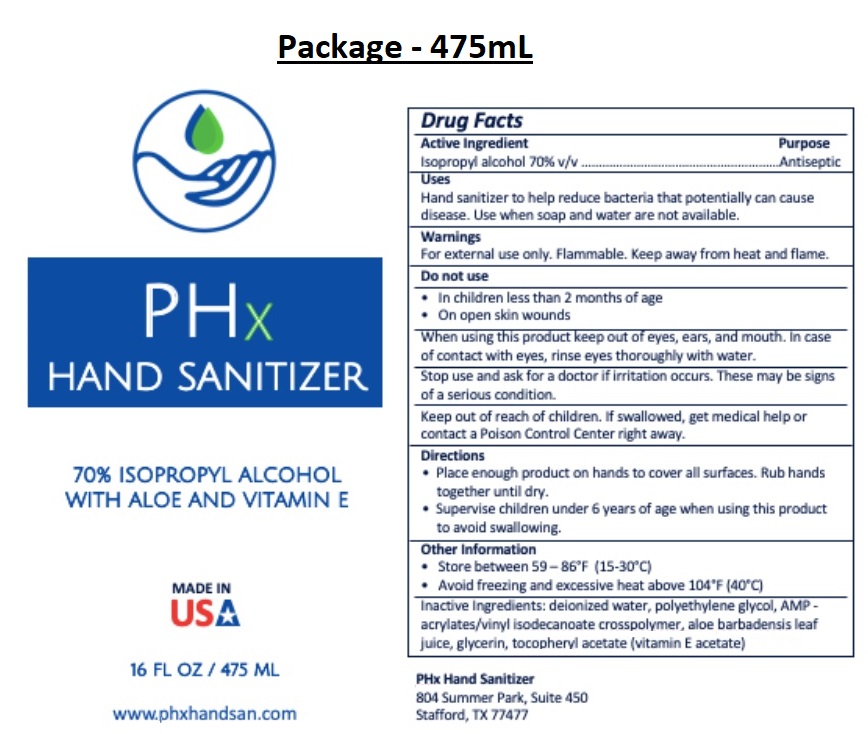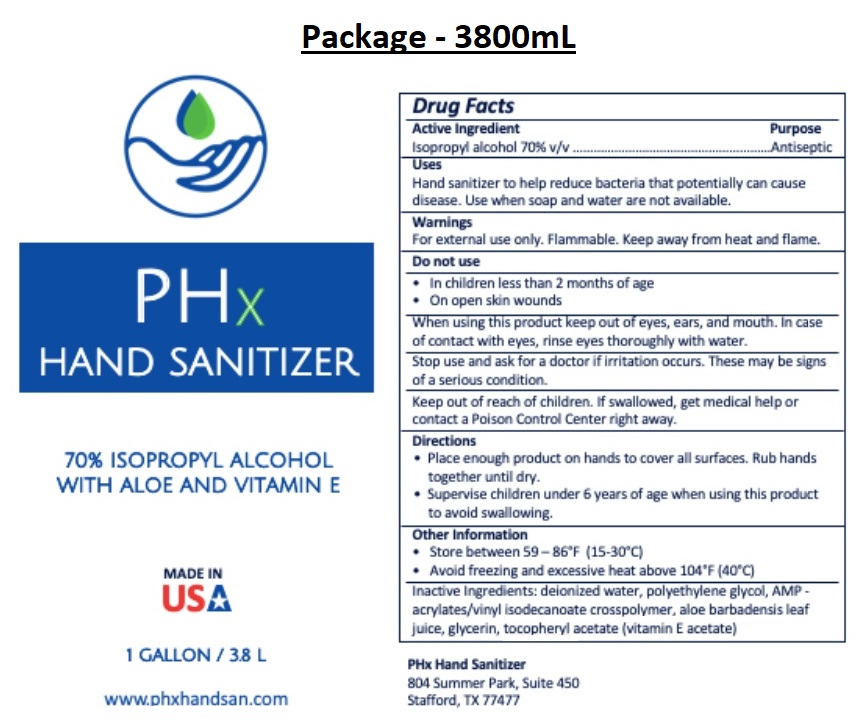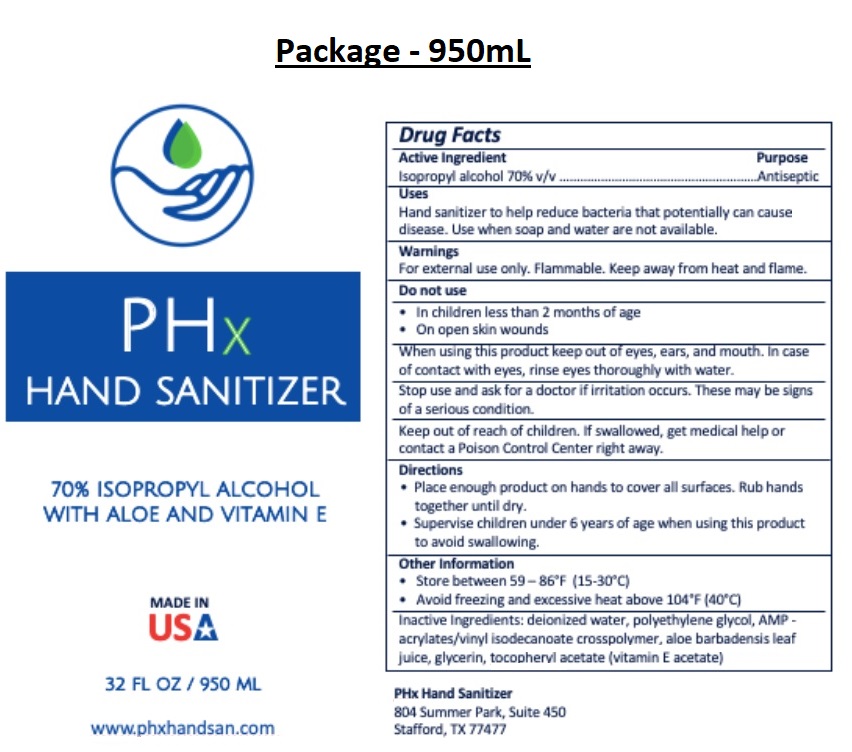 DRUG LABEL: PHx Hand Sanitizer
NDC: 80304-100 | Form: GEL
Manufacturer: Phx Hand Sanitizer Llc
Category: otc | Type: HUMAN OTC DRUG LABEL
Date: 20200901

ACTIVE INGREDIENTS: ISOPROPYL ALCOHOL 70 mL/100 mL
INACTIVE INGREDIENTS: WATER; POLYETHYLENE GLYCOL, UNSPECIFIED; ACRYLATES/VINYL ISODECANOATE CROSSPOLYMER (10000 MPA.S NEUTRALIZED AT 0.5%); ALOE VERA LEAF; GLYCERIN; .ALPHA.-TOCOPHEROL ACETATE

PHx HAND SANITIZER

Active Ingredient

Isopropyl alcohol 70% v/v

Purpose

Antiseptic

Uses

Hand sanitizer to help reduce bacteria that potentially can cause disease. Use when soap and water are not available.

Warnings

For external use only. Flammable. Keep away from heat and flame.

Do not use

• In children less than 2 months of age

• On open skin wounds

When using this product keep out of eyes, ears, and mouth. In case of contact with eyes, rinse eyes thoroughly with water.

Stop use and ask for a doctor if irritation occurs. These may be signs of a serious condition.

Keep out of reach of children. If swallowed, get medical help or contact a Poison Control Center right away.

Directions

• Place enough product on hands to cover all surfaces. Rub hands together until dry.

• Supervise children under 6 years of age when using this product to avoid swallowing.

Other information

• Store between 59-86˚F (15-30˚C)

• Avoid freezing and excessive heat above 104˚F (40˚C)

INACTIVE INGREDIENT

Inactive Ingredients: deionized water, polyethylene glycol, AMP - acrylates/vinyl isodecanoate crosspolymer, aloe barbadensis

leaf juice, glycerin, tocopheryl acetate (vitamin E acetate)

70% ISOPROPYL ALCOHOL WITH ALOE AND VITAMIN E

www.phxhandsan.com

MADE IN USA

PHx Hand Sanitizer

804 Summer Park, Suite 450

Stafford, TX 77477